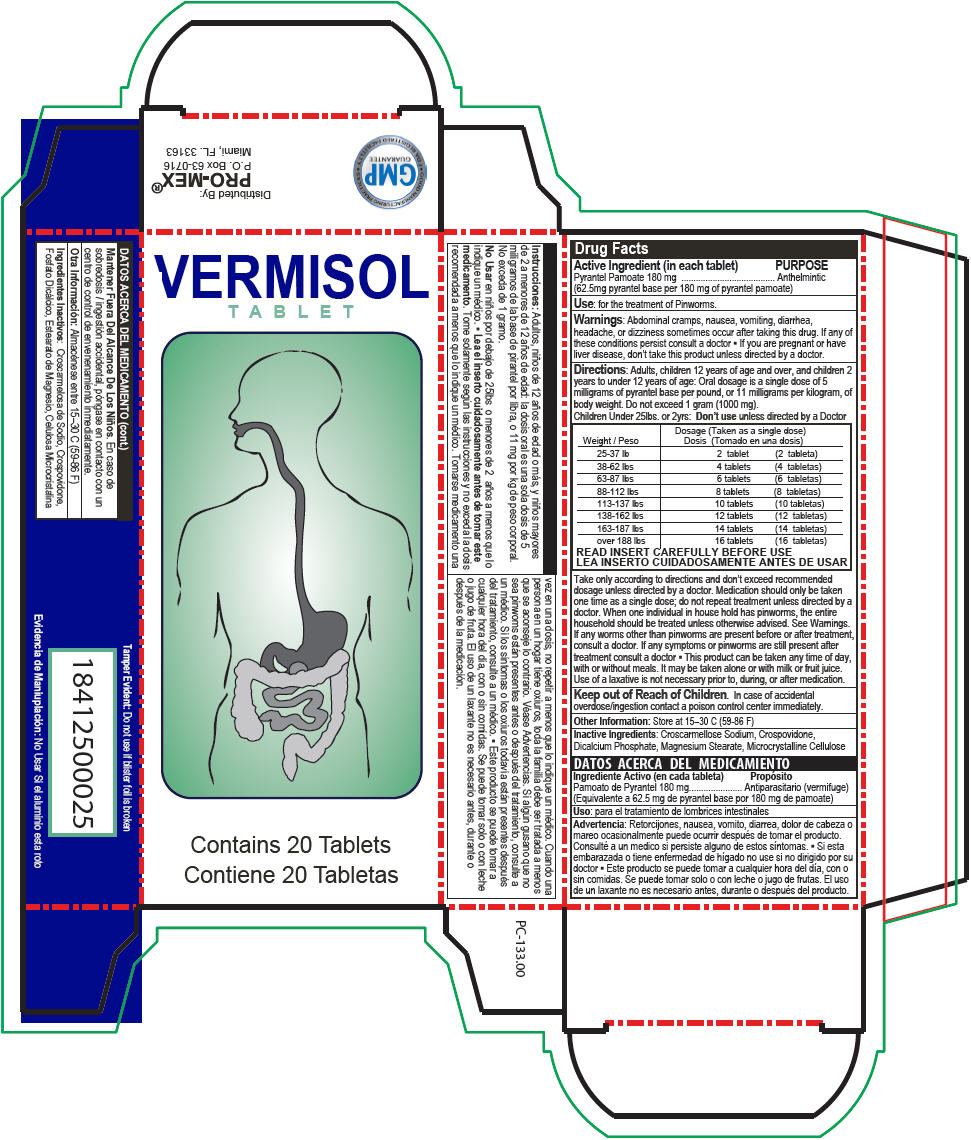 DRUG LABEL: Pyrantel Pamoate
NDC: 58988-1760 | Form: TABLET
Manufacturer: ProMex LLC
Category: otc | Type: HUMAN OTC DRUG LABEL
Date: 20180102

ACTIVE INGREDIENTS: Pyrantel Pamoate 180 mg/1 1
INACTIVE INGREDIENTS: Croscarmellose Sodium; Anhydrous Dibasic Calcium Phosphate; Magnesium Stearate; Microcrystalline Cellulose

Pyrantel Pamoate

Drug Facts

Active Ingredient (in each tablet)

Pyrantel Pamoate 180 mg (62.5mg pyrantel base per 180 mg of pyrantel pamoate)

PURPOSE

Anthelmintic

Use

for the treatment of Pinworms.

Warnings

ASK DOCTOR

Abdominal cramps, nausea, vomiting, diarrhea, headache, or dizziness sometimes occur after taking this drug. If any of these conditions persist consult a doctor

- If you are pregnant or have liver disease, don't take this product unless directed by a doctor.

Directions

Adults, children 12 years of age and over, and children 2 years to under 12 years of age: Oral dosage is a single dose of 5 milligrams of pyrantel base per pound, or 11 milligrams per kilogram, of body weight. Do not exceed 1 gram (1000 mg).

Weight | Dosage (Taken as a single dose)
25-37 lb | 2 tablet
38-62 lbs | 4 tablets
63-87 lbs | 6 tablets
88-112 lbs | 8 tablets
113-137 lbs | 10 tablets
138-162 lbs | 12 tablets
163-187 lbs | 14 tablets
over 188 lbs | 16 tablets
READ INSERT CAREFULLY BEFORE USE

Take only according to directions and don't exceed recommended dosage unless directed by a doctor. Medication should only be taken one time as a single dose; do not repeat treatment unless directed by a doctor. When one individual in house hold has pinworms, the entire household should be treated unless otherwise advised. See Warnings. If any worms other than pinworms are present before or after treatment, consult a doctor. If any symptoms or pinworms are still present after treatment consult a doctor

- This product can be taken any time of day, with or without meals. It may be taken alone or with milk or fruit juice. Use of a laxative is not necessary prior to, during, or after medication.

Keep out of Reach of Children. In case of accidental overdose/ingestion contact a poison control center immediately.

Inactive Ingredients

Croscarmellose Sodium, Crospovidone, Dicalcium Phosphate, Magnesium Stearate, Microcrystalline Cellulose

PRINCIPAL DISPLAY PANEL - 20 Tablet Blister Pack Carton

VERMISOL
TABLET

Contains 20 Tablets